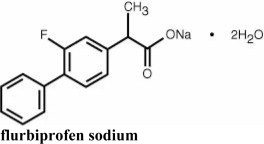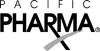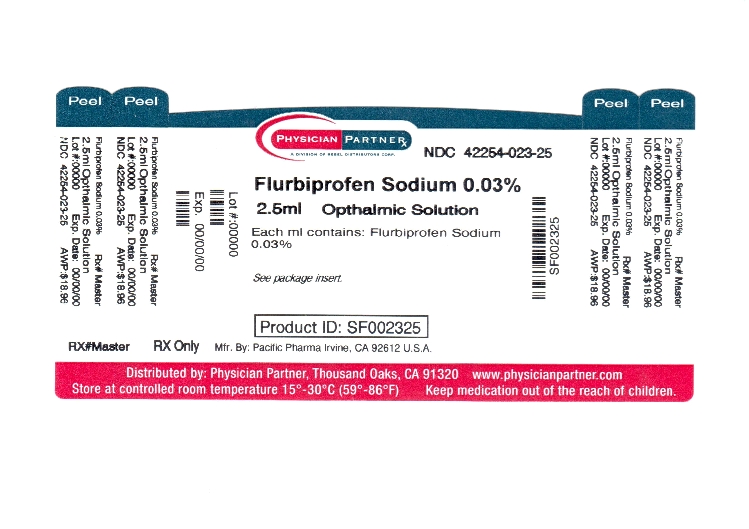 DRUG LABEL: FLURBIPROFEN SODIUM
NDC: 42254-023 | Form: SOLUTION/ DROPS
Manufacturer: Rebel Distributors Corp
Category: prescription | Type: HUMAN PRESCRIPTION DRUG LABEL
Date: 20111213

ACTIVE INGREDIENTS: flurbiprofen sodium 0.3 mg/1 mL
INACTIVE INGREDIENTS: thimerosal; citric acid monohydrate; edetate disodium; polyvinyl alcohol; potassium chloride; water; sodium chloride; sodium citrate; hydrochloric acid; sodium hydroxide

Flurbiprofen Sodium
Ophthalmic Solution, USP 0.03%

Sterile

DESCRIPTION

Flurbiprofen sodium ophthalmic solution, USP 0.03% is a sterile topical nonsteroidal anti-inflammatory product for ophthalmic use.

Chemical Name: Sodium (±)-2-(2-fluoro-4-biphenylyl)-propionate dihydrate.

Structural Formula:

Contains: Active: flurbiprofen sodium 0.03% (0.3mg/mL).

Preservative: thimerosal 0.005%. Inactives: citric acid; edetate disodium; polyvinyl alcohol 1.4%; potassium chloride; purified water; sodium chloride; and sodium citrate. May also contain hydrochloric acid and/or sodium hydroxide to adjust the pH. The pH of flurbiprofen sodium ophthalmic solution 0.03% is 6.0 to 7.0. It has an osmolality of 260 - 330 mOsm/kg.

CLINICAL PHARMACOLOGY

Flurbiprofen sodium is one of a series of phenylalkanoic acids that have shown analgesic, antipyretic, and anti-inflammatory activity in animal inflammatory diseases. Its mechanism of action is believed to be through inhibition of the cyclo-oxygenase enzyme that is essential in the biosynthesis of prostaglandins.

Prostaglandins have been shown in many animal models to be mediators of certain kinds of intraocular inflammation. In studies performed on animal eyes, prostaglandins have been shown to produce disruption of the blood-aqueous humor barrier, vasodilatation, increased vascular permeability, leukocytosis, and increased intraocular pressure.

Prostaglandins also appear to play a role in the miotic response produced during ocular surgery by constricting the iris sphincter independently of cholinergic mechanisms. In clinical studies, flurbiprofen sodium ophthalmic solution 0.03% has been shown to inhibit the miosis induced during the course of cataract surgery. Results from clinical studies indicate that flurbiprofen sodium has no significant effect upon intraocular pressure.

INDICATIONS AND USAGE

Flurbiprofen sodium ophthalmic solution 0.03% is indicated for the inhibition of intraoperative miosis.

CONTRAINDICATIONS

Flurbiprofen sodium ophthalmic solution 0.03% is contraindicated in individuals who are hypersensitive to any components of the medication.

WARNINGS

With nonsteroidal anti-inflammatory drugs, there exists the potential for increased bleeding due to interference with thrombocyte aggregation. There have been reports that flurbiprofen sodium ophthalmic solution 0.03% may cause increased bleeding of ocular tissues including hyphemas in conjunction with ocular surgery.

There exists the potential for cross-sensitivity to acetylsalicylic acid and other nonsteroidal anti-inflammatory drugs. Therefore, caution should be used when treating individuals who have previously exhibited sensitivities to these drugs.

PRECAUTIONS

GENERAL PRECAUTIONS

General: Wound healing may be delayed with the use of flurbiprofen sodium ophthalmic solution 0.03%.

It is recommended that flurbiprofen sodium ophthalmic solution 0.03% be used with caution in surgical patients with known bleeding tendencies or who are receiving other medications which may prolong bleeding time.

DRUG INTERACTIONS

Drug interactions: Interaction of flurbiprofen sodium ophthalmic solution 0.03% with other topical ophthalmic medications has not been fully investigated.

Although clinical studies with acetylcholine chloride and animal studies with acetylcholine chloride or carbachol revealed no interference, and there is no known pharmacological basis for an interaction, there have been reports that acetylcholine chloride and carbachol have been ineffective when used in patients treated with flurbiprofen sodium ophthalmic solution 0.03%.

CARCINOGENESIS AND MUTAGENESIS AND IMPAIRMENT OF FERTILITY

Carcinogenesis, Mutagenesis, Impairment of fertility: Long-term studies in mice and/or rats have shown no evidence of carcinogenicity with flurbiprofen. Long-term mutagenicity studies in animals have not been performed.

Pregnancy:

Pregnancy category C. Flurbiprofen has been shown to be embryocidal, delay parturition, prolong gestation, reduce weight, and/or slightly retard growth of fetuses when given to rats in daily oral doses of 0.4 mg/kg (approximately 333 times the human daily topical dose) and above.

NURSING MOTHERS

Nursing mothers: It is not known whether this drug is excreted in human milk. Because many drugs are excreted in human milk and because of the potential for serious adverse reactions in nursing infants from flurbiprofen sodium, a decision should be made whether to discontinue nursing or to discontinue the drug, taking into account the importance of the drug to the mother.

PEDIATRIC USE

Pediatric use: Safety and effectiveness in pediatric patients have not been established.

GERIATRIC USE

Geriatric use: No overall differences in safety or effectiveness have been observed between elderly and younger patients.

ADVERSE REACTIONS

Transient burning and stinging upon instillation and other minor symptoms of ocular irritation have been reported with the use of flurbiprofen sodium ophthalmic solution 0.03%. Other adverse reactions reported with the use of flurbiprofen sodium ophthalmic solution 0.03% include: fibrosis, miosis, and mydriasis.

Increased bleeding tendency of ocular tissues in conjunction with ocular surgery has also been reported.

OVERDOSAGE

Overdosage will not ordinarily cause acute problems. If accidentally ingested, drink fluids to dilute.

DOSAGE AND ADMINISTRATION

A total of four (4) drops of flurbiprofen sodium ophthalmic solution 0.03% should be administered by instilling one (1) drop approximately every 1/2 hour beginning 2 hours before surgery.

HOW SUPPLIED

Flurbiprofen sodium ophthalmic solution, USP is available for topical ophthalmic administration as a 0.03% sterile solution, and is supplied in a white opaque low density polyethylene bottle with a controlled dropper tip and a gray high impact polystyrene cap in the following size:

2.5 mL in 5 mL bottle - NDC 42254-023-25

Note: Store at 15°-25°C (59°-77°F).

Rx Only

Revised January 2004

© 2004 PACIFIC PHARMA
Irvine, CA 92612, U.S.A.

71587PY11P

Relabeled by:

Rebel Distributors Corp

Thousand Oaks, CA 91320